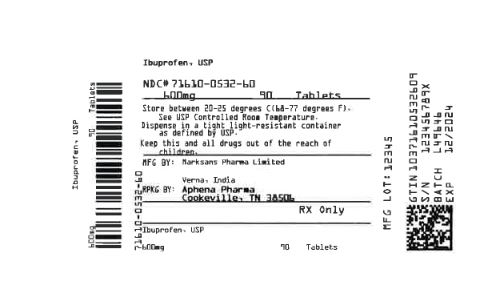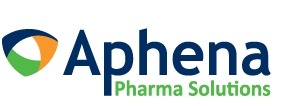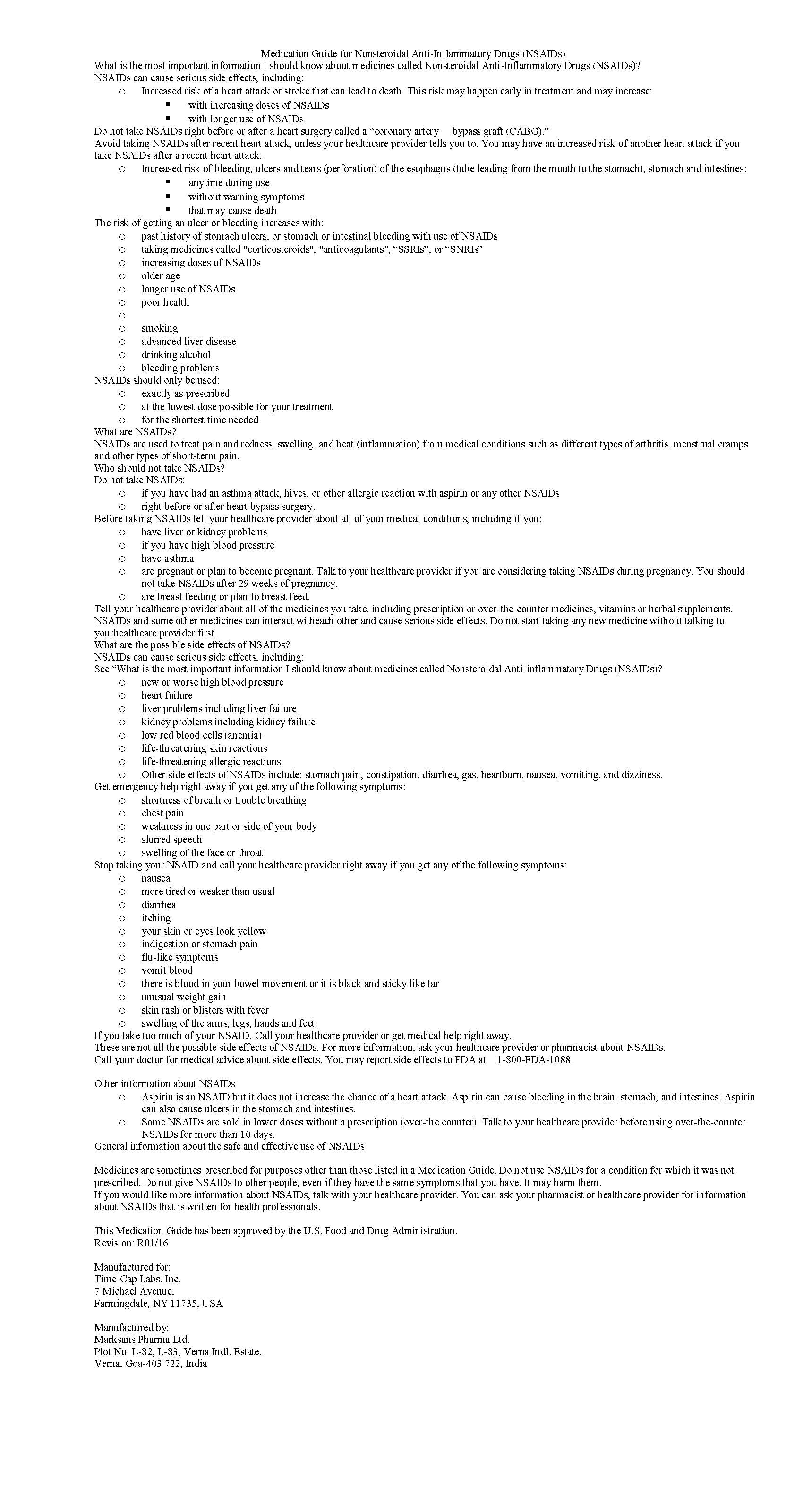 DRUG LABEL: IBUPROFEN
NDC: 71610-532 | Form: TABLET, FILM COATED
Manufacturer: Aphena Pharma Solutions - Tennessee, LLC
Category: prescription | Type: HUMAN PRESCRIPTION DRUG LABEL
Date: 20210420

ACTIVE INGREDIENTS: IBUPROFEN 600 mg/1 1
INACTIVE INGREDIENTS: SILICON DIOXIDE; CROSCARMELLOSE SODIUM; MAGNESIUM STEARATE; CELLULOSE, MICROCRYSTALLINE; POLYETHYLENE GLYCOL, UNSPECIFIED; POLYVINYL ALCOHOL; STARCH, PREGELATINIZED CORN; TALC; TITANIUM DIOXIDE

IBUPROFEN 400 MG - 600 MG AND 800 MG TABLETS

HOW SUPPLIED

400mg (white to of white, round, biconvex, film coated tablets debossed with '121' on one side and plain on the other side) Bottles of 100 & 500

HOW SUPPLIED

600mg (white to off white, capsule shaped, biconvex, film coated tablets debossed with '122' on one side and plain on the other side) Bottles of 30, 50, 100 & 500

HOW SUPPLIED

800 mg (white to off-white, capsule shaped, biconvex, film-coated tablets debossed with ‘123’ on one side and plain on other side)

Repackaging Information

Please reference the How Supplied section listed above for a description of individual tablets. This drug product has been received by Aphena Pharma - TN in a manufacturer or distributor packaged configuration and repackaged in full compliance with all applicable cGMP regulations. The package configurations available from Aphena are listed below:

Count | 600 mg
90 | 71610-532-60
180 | 71610-532-80
270 | 71610-532-92

Store between 20°-25°C (68°-77°F). See USP Controlled Room Temperature. Dispense in a tight light-resistant container as defined by USP. Keep this and all drugs out of the reach of children.

Repackaged by:
Cookeville, TN 38506
20210420JH

PRINCIPAL DISPLAY PANEL - 600 mg

NDC 71610-532 - Ibuprofen, USP 600 mg Tablets - Rx Only